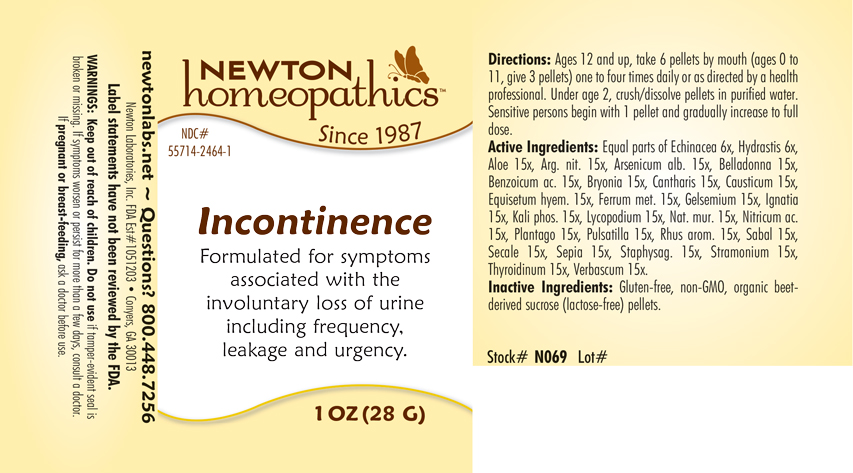 DRUG LABEL: Incontinence
NDC: 55714-2464 | Form: PELLET
Manufacturer: Newton Laboratories, Inc.
Category: homeopathic | Type: HUMAN OTC DRUG LABEL
Date: 20250207

ACTIVE INGREDIENTS: ALOE 15 [hp_X]/1 g; SILVER NITRATE 15 [hp_X]/1 g; ARSENIC TRIOXIDE 15 [hp_X]/1 g; ATROPA BELLADONNA 15 [hp_X]/1 g; BENZOIC ACID 15 [hp_X]/1 g; BRYONIA ALBA ROOT 15 [hp_X]/1 g; LYTTA VESICATORIA 15 [hp_X]/1 g; CAUSTICUM 15 [hp_X]/1 g; EQUISETUM HYEMALE 15 [hp_X]/1 g; IRON 15 [hp_X]/1 g; GELSEMIUM SEMPERVIRENS ROOT 15 [hp_X]/1 g; STRYCHNOS IGNATII SEED 15 [hp_X]/1 g; POTASSIUM PHOSPHATE, DIBASIC 15 [hp_X]/1 g; LYCOPODIUM CLAVATUM SPORE 15 [hp_X]/1 g; SODIUM CHLORIDE 15 [hp_X]/1 g; NITRIC ACID 15 [hp_X]/1 g; PLANTAGO MAJOR 15 [hp_X]/1 g; ANEMONE PULSATILLA 15 [hp_X]/1 g; RHUS AROMATICA ROOT BARK 15 [hp_X]/1 g; SAW PALMETTO 15 [hp_X]/1 g; CLAVICEPS PURPUREA SCLEROTIUM 15 [hp_X]/1 g; SEPIA OFFICINALIS JUICE 15 [hp_X]/1 g; DELPHINIUM STAPHISAGRIA SEED 15 [hp_X]/1 g; DATURA STRAMONIUM 15 [hp_X]/1 g; THYROID, UNSPECIFIED 15 [hp_X]/1 g; VERBASCUM THAPSUS 15 [hp_X]/1 g; ECHINACEA, UNSPECIFIED 6 [hp_X]/1 g; GOLDENSEAL 6 [hp_X]/1 g
INACTIVE INGREDIENTS: SUCROSE

Incontinence 2464P

INDICATIONS & USAGE SECTION

Formulated for symptoms associated with the involuntary loss of urine including frequency, leakage and urgency.

DOSAGE & ADMINISTRATION SECTION

Directions: Ages 12 and up, take 6 pellets by mouth (ages 0 to 11, give 3 pellets) one to four times daily or as directed by a health professional. Under age 2, crush/dissolve pellets in purified water. Sensitive persons begin with 1 pellet and gradually increase to full dose.

OTC - ACTIVE INGREDIENT SECTION

Equal parts of Echinacea 6x, Hydrastis canadensis 6x,Aloe 15x, Argentum nitricum 15x, Arsenicum album 15x, Belladonna 15x, Benzoicum acidum 15x, Bryonia 15x, Cantharis 15x, Causticum 15x, Equisetum hyemale 15x, Ferrum metallicum 15x, Gelsemium sempervirens 15x, Ignatia amara 15x, Kali phosphoricum 15x, Lycopodium clavatum 15x, Natrum muriaticum 15x, Nitricum acidum 15x, Plantago major 15x, Pulsatilla 15x, Rhus aromatica 15x, Sabal serrulata 15x, Secale cornutum 15x, Sepia 15x, Staphysagria 15x, Stramonium 15x, Thyroidinum 15x, Verbascum thapsus 15x.

OTC - PURPOSE SECTION

Formulated for symptoms associated with the involuntary loss of urine including frequency, leakage and urgency.

INACTIVE INGREDIENT SECTION

Inactive Ingredients: Gluten-free, non-GMO, organic beet-derived sucrose (lactose-free) pellets.

QUESTIONS SECTION

newtonlabs.net – Questions? 800.448.7256

Newton Laboratories, Inc. FDA Est # 1051203 - Conyers, GA 30013

WARNINGS SECTION

WARNINGS: Keep out of reach of children. Do not use if tamper-evident seal is broken or missing. If symptoms worsen or persist for more than a few days, consult a doctor. If pregnant or breast-feeding, ask a doctor before use

OTC - PREGNANCY OR BREAST FEEDING SECTION

If pregnant or breast-feeding, ask a doctor before use

OTC - KEEP OUT OF REACH OF CHILDREN SECTION

Keep out of reach of children.